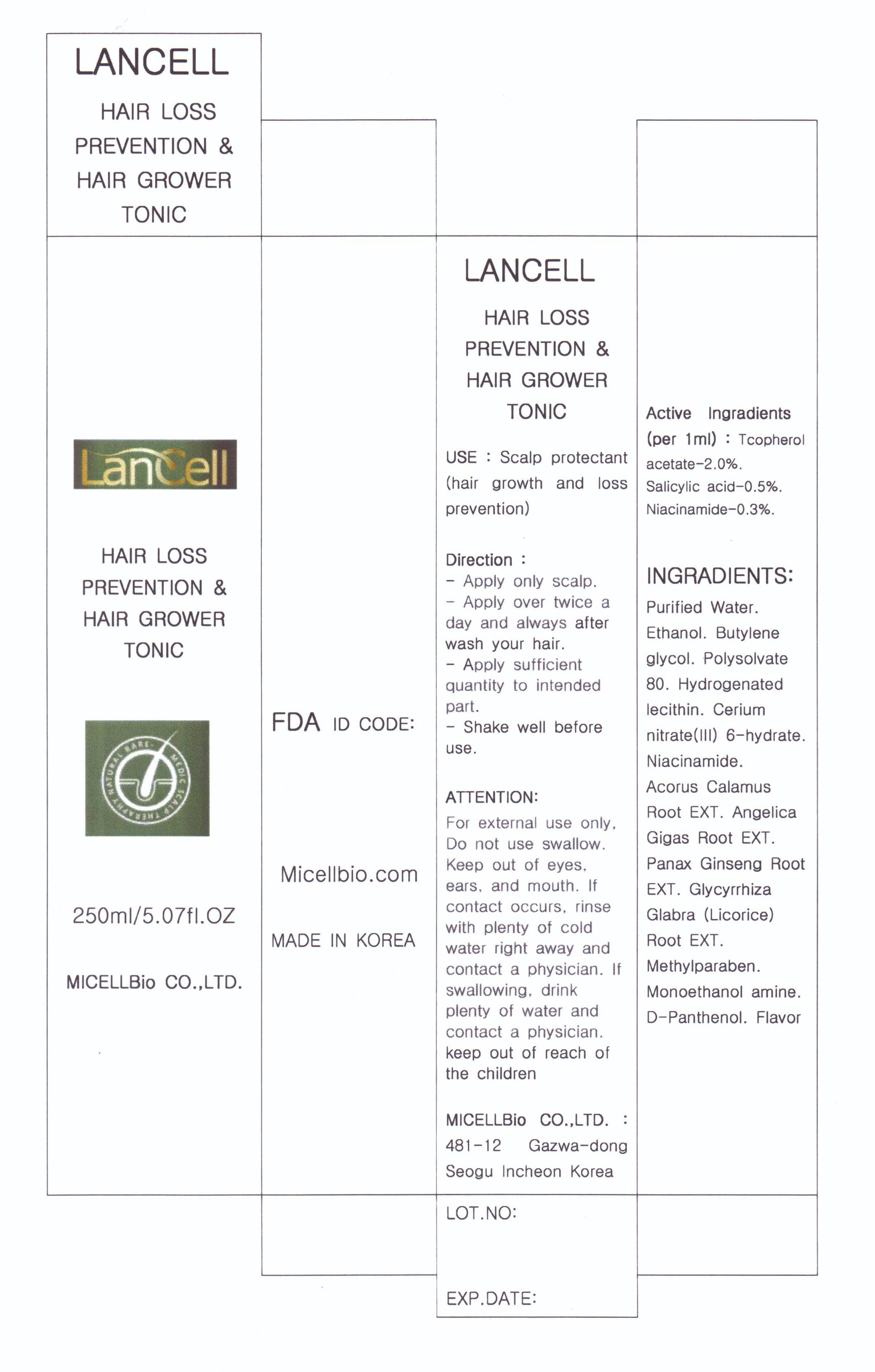 DRUG LABEL: Lancell hair loss prevention hair grower tonic
NDC: 76084-2001 | Form: LIQUID
Manufacturer: MICELLBio Co., Ltd
Category: otc | Type: HUMAN OTC DRUG LABEL
Date: 20110408

ACTIVE INGREDIENTS: SALICYLIC ACID 0.005 mL/1 mL; NIACINAMIDE 0.003 mL/1 mL
INACTIVE INGREDIENTS: WATER; BUTYLENE GLYCOL; POLYSORBATE 80; HYDROGENATED SOYBEAN LECITHIN; ACORUS CALAMUS ROOT; ANGELICA GIGAS ROOT; PANAX GINSENG ROOT WATER; GLYCYRRHIZA GLABRA; METHYLPARABEN; MONOETHANOLAMINE; PANTHENOL

Drug Facts

active ingredient: salicylic acid, niacinamide, tocopherol acetate

inactive ingredient: d-water, ethanol, butylene glycol, polysorbate 80, hydrogenated lecithin, cerium nitrate(III) 6-hydrate, acorus calamus root extract, angelica gigas root extract, panax ginseng root extract, glycyrrhiza glabra root extract, methylparaben, monoethanol amine, d-panthenol, flavor

PURPOSE

scalp protectant (hair growth and loss prevention)

keep out of reach of the children

INDICATIONS AND USAGE

- shake well before use
- apply sufficient quantity to intended part

WARNINGS

- for external use only
- do not swallow
- keep out of eyes, ears and mouth

DOSAGE AND ADMINISTRATION

- apply only for scalp
- apply more than twice a day after washing hair